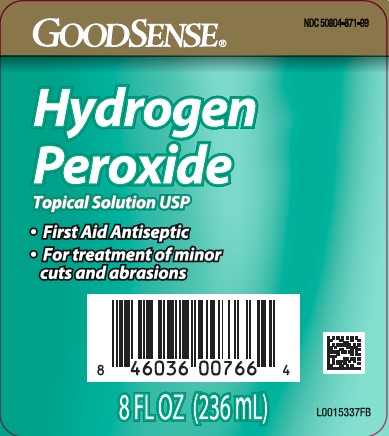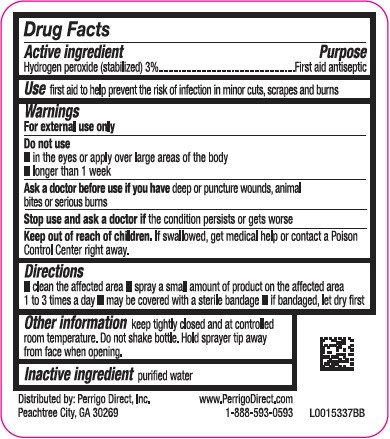 DRUG LABEL: Hydrogen Peroxide
NDC: 50804-871 | Form: SOLUTION
Manufacturer: Perrigo Direct, Inc
Category: otc | Type: HUMAN OTC DRUG LABEL
Date: 20260219

ACTIVE INGREDIENTS: HYDROGEN PEROXIDE 30 mg/1 mL
INACTIVE INGREDIENTS: WATER

Good Sense 871.001/871AA
3% Hydrogen Peroxide

Active ingredient

Hydrogen peroxide (stabilized) 3%

Purpose

First Aid Antiseptic

Use

- first aid to help prevent the risk of infection in minor cuts, scrapes and burns

Warnings

For external use only

Do not use

- in the eyes or apply over large areas of the body
- longer than 1 week

Ask a doctor before use if you have

deep or pucture wounds, animal bites or serious burns

Stop Use and ask a doctor if

- the condition persists or gets worse

Keep out of reach of children.

If swallowed, get medical help or contact a Poison Control Center right away.

Directions

- clean the affected area
- spray a small amount of the product on the affected area 1 to 3 times a day
- may be covered with a sterile bandage
- if bandaged, let dry first

Other Information

keep tightly closed and at controlled room temperature. Do not shake bottle. Hold sprayer tip away from face when opening.

Inactive ingredient

purified water

ADVERSE REACTION

Distrubuted by: Perrigo Direct, Inc

Peachtree City, GA 30269

www.PerrigoDirect.com

1-888-593-0593

Principal Display Panel

NDC 50804-871-99

GoodSense®

Hydrogen

Peroxide

Topical Solution USP

- First Aid Antiseptic
- For treatment of minor cuts and abrasions

8 FL OZ (236 mL)